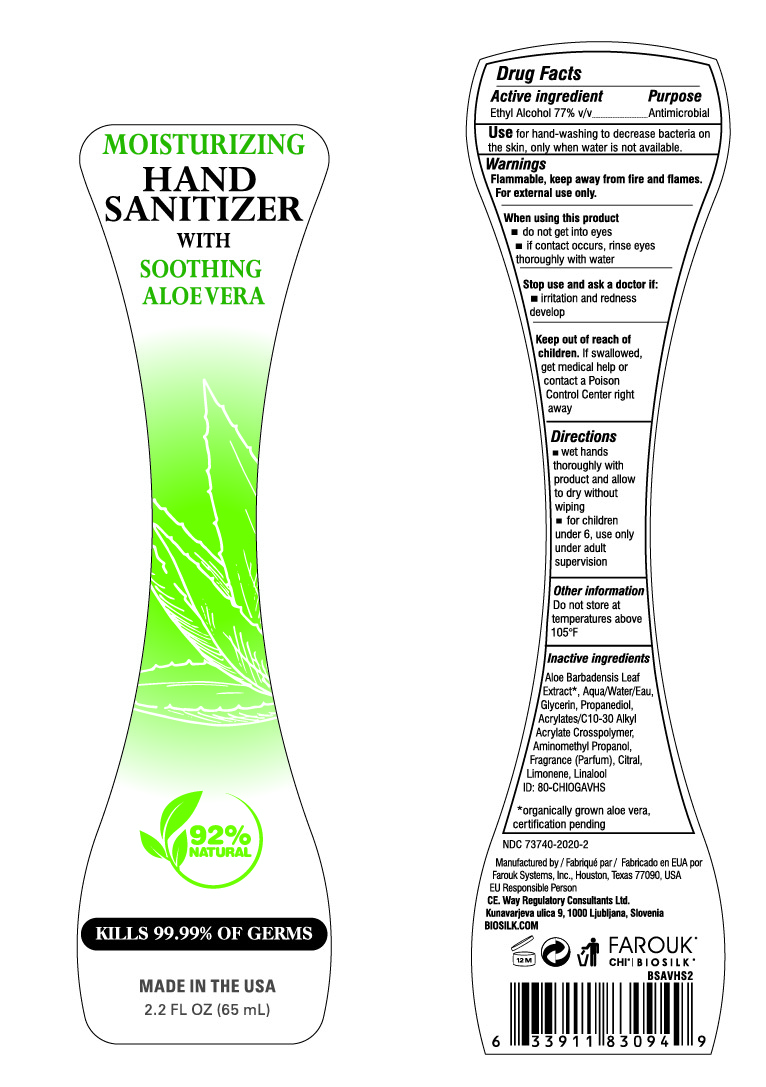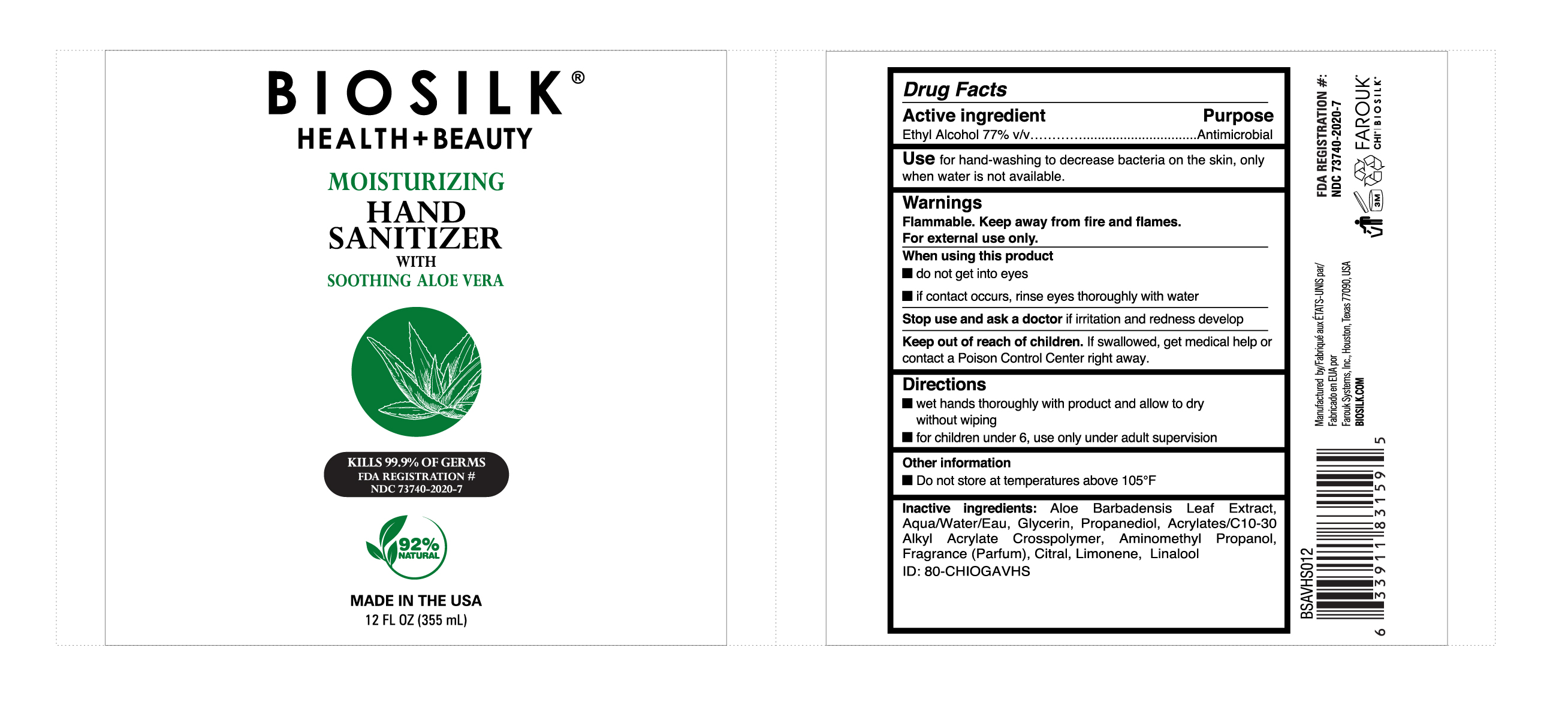 DRUG LABEL: BioSilk Hand Sanitizer
NDC: 73740-2020 | Form: GEL
Manufacturer: Farouk Systems, Inc.
Category: otc | Type: HUMAN OTC DRUG LABEL
Date: 20200909

ACTIVE INGREDIENTS: ALCOHOL 77 g/100 g
INACTIVE INGREDIENTS: CITRAL 0.0275 g/100 g; AMINOMETHYL PROPANEDIOL 0.095 g/100 g; ALOE VERA LEAF 28.5 g/100 g; PROPANEDIOL 2 g/100 g; FRAGRANCE LAVENDER & CHIA F-153480 0.0715 g/100 g; (C10-C30)ALKYL METHACRYLATE ESTER 0.4 g/100 g; LINALOOL, (+)- 0.00475 g/100 g; WATER 6.255 g/100 g; GLYCERIN 2 g/100 g; LIMONENE, (+)- 0.14625 g/100 g

BioSilk Hand Sanitizer

Dosage & Administration

Active ingredient Purpose
Ethyl Alcohol 77% v/v Antimicrobial

Use for hand-washing to decrease bacteria on
the skin, only when water is not available.

Inactive Ingredients

Aloe Barbadensis Leaf
Extract*, Aqua/Water/Eau,
Glycerin, Propanediol,
Acrylates/C10-30 Alkyl
Acrylate Crosspolymer,
Aminomethyl Propanol,
Fragrance (Parfum), Citral,
Limonene, Linalool
ID: 80-CHIOGAVHS
*organically grown aloe vera,
certification pending

Active Ingredients

Active ingredient Purpose
Ethyl Alcohol 77% v/v Antimicrobial

Route, Methos and Frequency of Administration

Use for hand-washing to decrease bacteria on
the skin, only when water is not available.

Directions
wet hands
thoroughly with
product and allow
to dry without
wiping
for children
under 6, use only
under adult
supervision

Warnings and Precautions

Warnings
Flammable, keep away from fire and flames.
For external use only.
When using this product
do not get into eyes
if contact occurs, rinse eyes
thoroughly with water
Stop use and ask a doctor if:
irritation and redness
develop
Keep out of reach of
children. If swallowed,
get medical help or
contact a Poison
Control Center right
away

Storage and Handling

Other information
Do not store at
temperatures above
105°F

Indications & Usage

Use for hand-washing to decrease bacteria on
the skin, only when water is not available.

Directions
wet hands
thoroughly with
product and allow
to dry without
wiping
for children
under 6, use only
under adult
supervision

Warnings

Flammable, keep away from fire and flames.
For external use only.
When using this product
do not get into eyes
if contact occurs, rinse eyes
thoroughly with water
Stop use and ask a doctor if:
irritation and redness
develop
Keep out of reach of
children. If swallowed,
get medical help or
contact a Poison
Control Center right
away

OTC - Keep out of reach of Children

Keep out of reach of
children. If swallowed,
get medical help or
contact a Poison
Control Center right
away

Purpose

Use for hand-washing to decrease bacteria on
the skin, only when water is not available.

Principal Display Panel

BioSilk

Moisturizing Hand Sanitizer'

With Soothing Aloe Vera

92% Natural

KILLS 99.99% OF GERMS

MADE IN THE USA

2.2 FL OZ (65 mL)